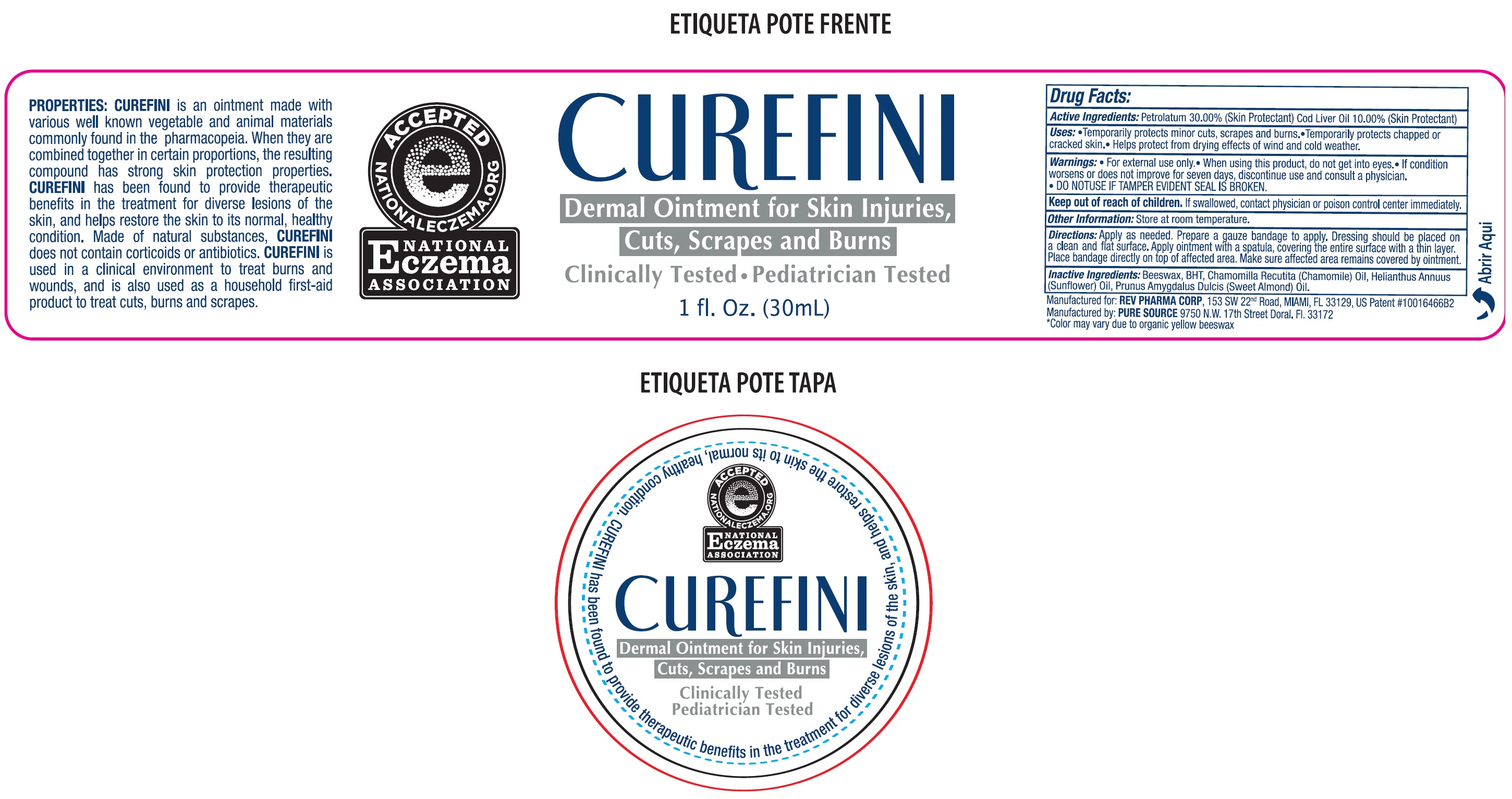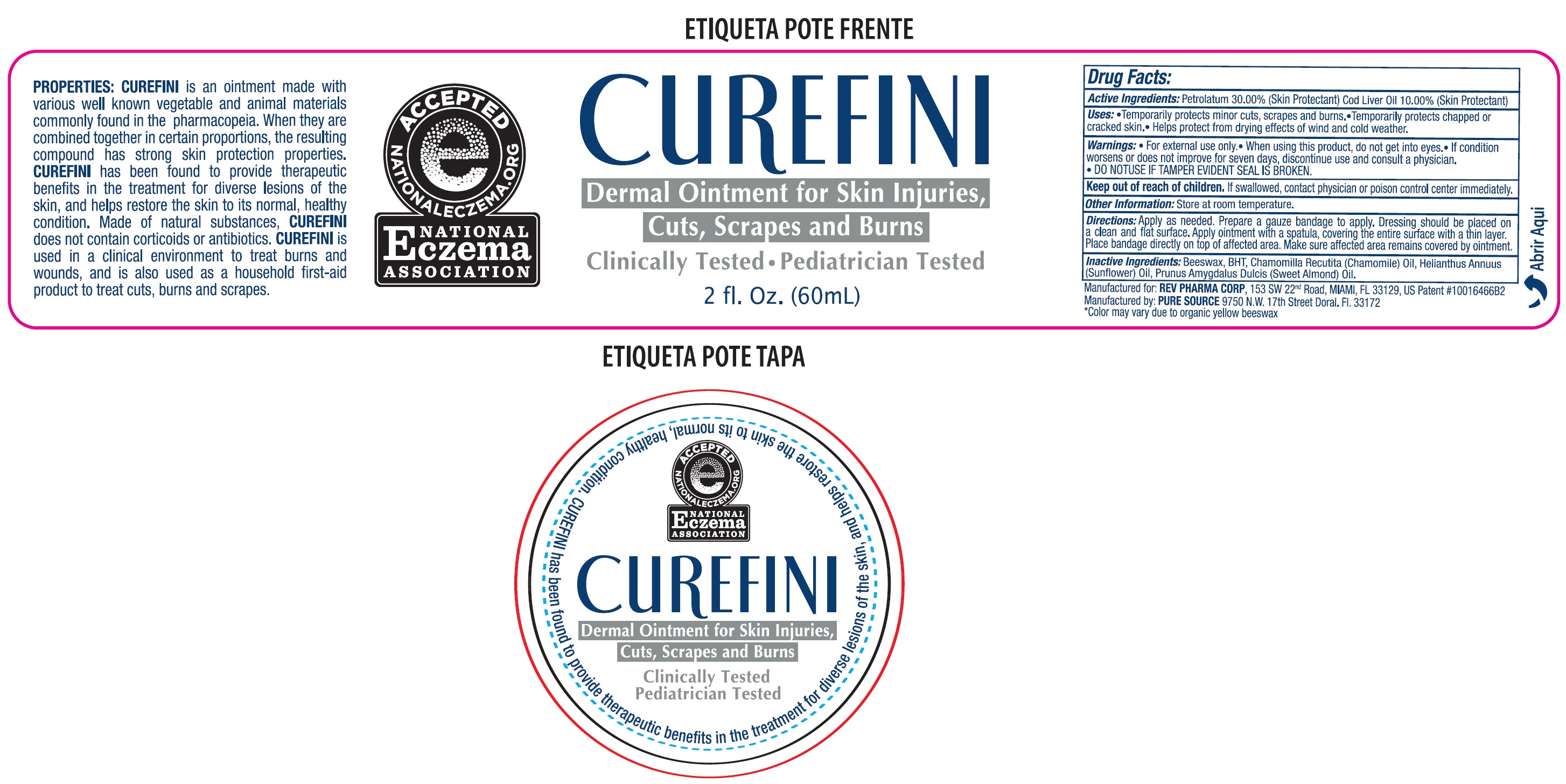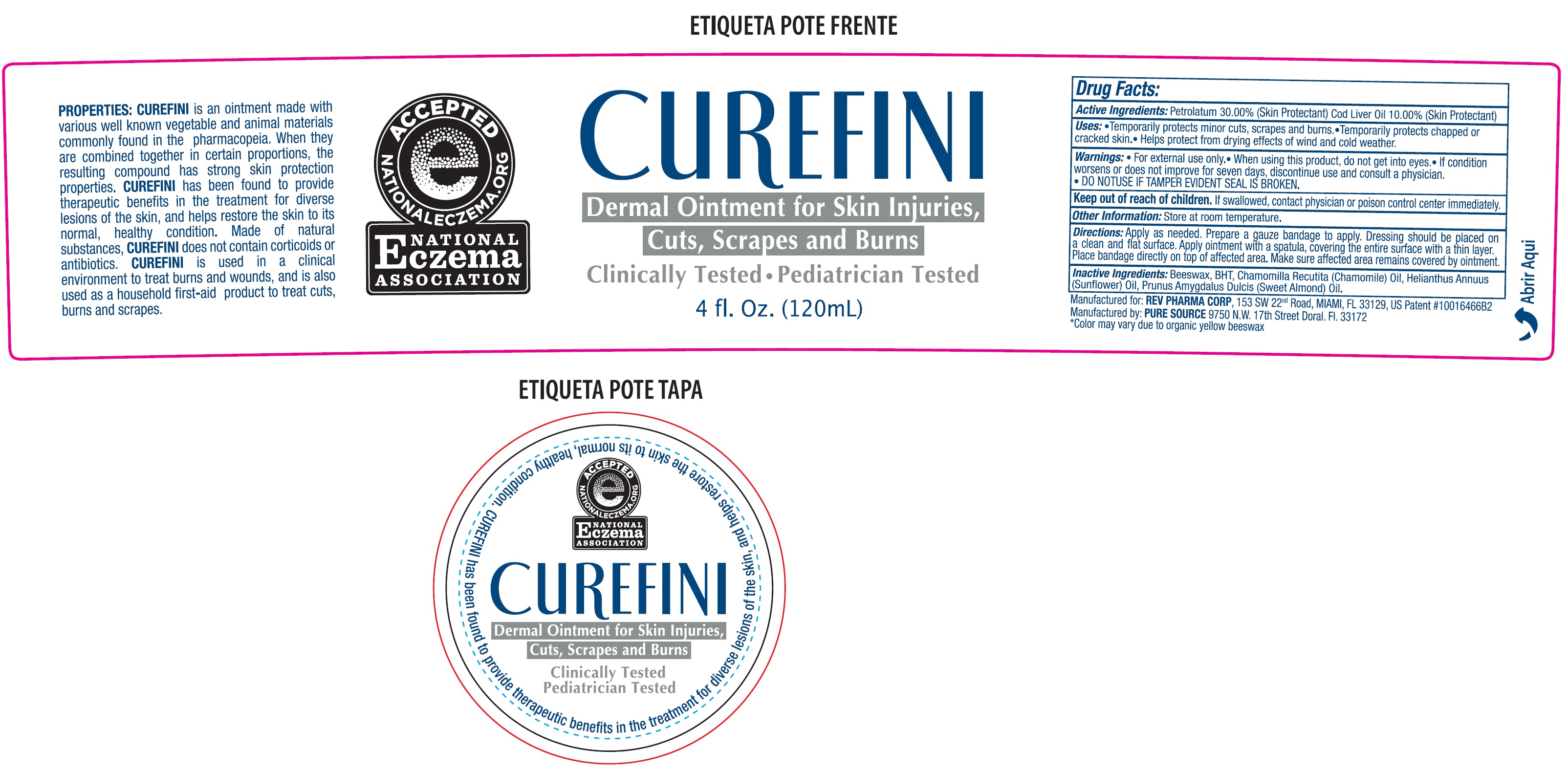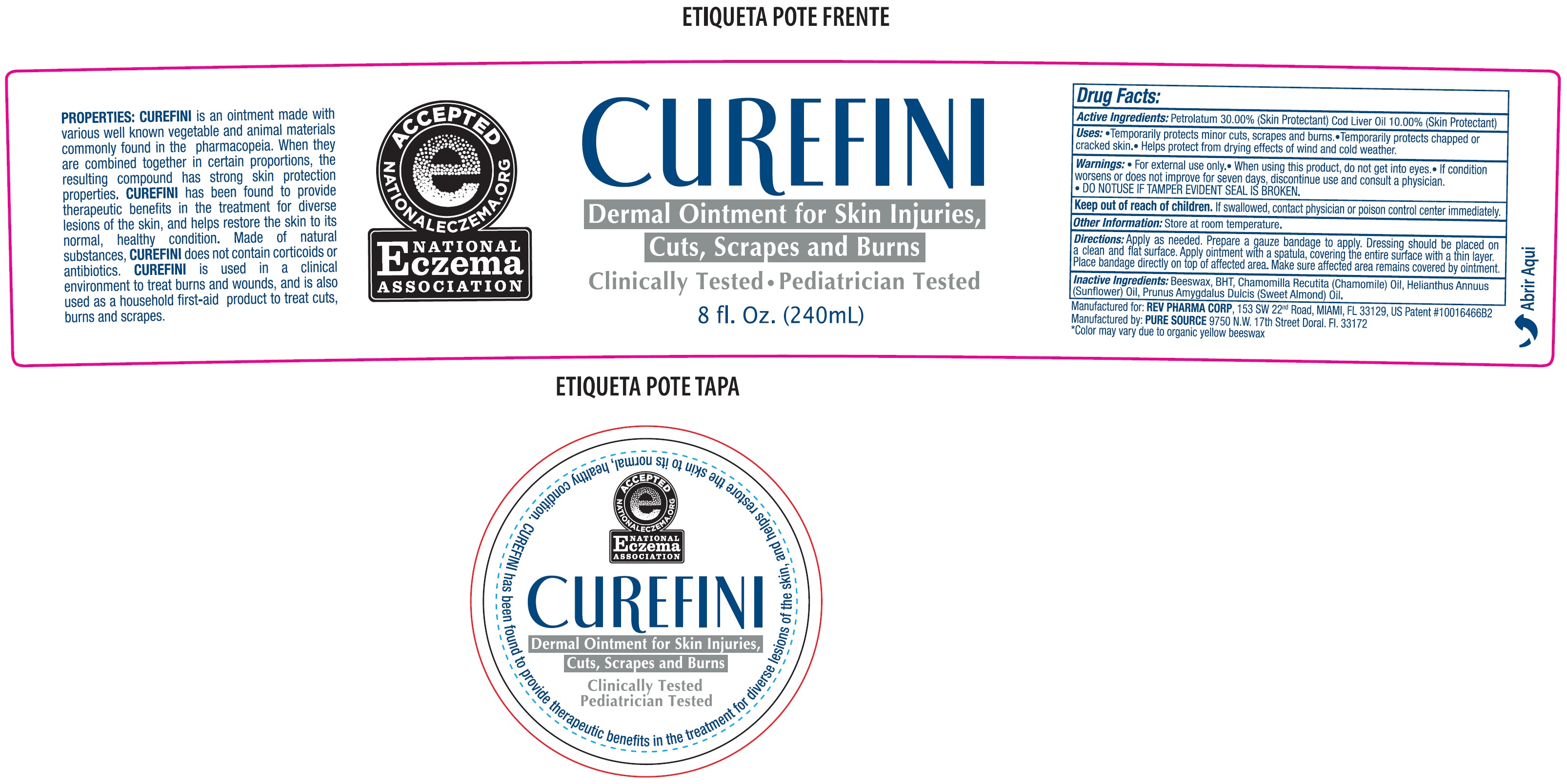 DRUG LABEL: CUREFINI Dermal
NDC: 69981-704 | Form: CREAM
Manufacturer: Rev Pharma Corporation
Category: otc | Type: HUMAN OTC DRUG LABEL
Date: 20231110

ACTIVE INGREDIENTS: PETROLATUM 300 mg/1 mL; COD LIVER OIL 100 mg/1 mL
INACTIVE INGREDIENTS: YELLOW WAX; CHAMOMILE; HELIANTHUS ANNUUS FLOWERING TOP; ALMOND OIL

CUREFINI Dermal Ointment

Active Ingredients:

Petrolatum 30.00% Cod Liver Oil 10.00%

PURPOSE

(Skin Protectant)

Uses:

- Temporarily protects of minor cuts, scrapes and burns.
- Temporarily protects chapped or cracked skin.
- Helps protect from drying effects of wind and cold weather.

Warnings:

- For external use only.

When using this product,

- do not get into eyes.
- If condition worsens or does not improve for seven days,discontinue use and consult a physician.
- DO NOTUSE IF TAMPER EVIDENT SEAL IS BROKEN.

Keep out of reach of children.

If swallowed, contact physician or poison control center immediately.

Other Information:

- Store at room temperature.

Directions:

Apply as needed. Prepare a gauze bandage to apply. Dressing should be placed on a clean and flat surface. Apply ointment with a spatula, covering the entire surface with a thin layer. Place bandage directly on top of affected area. Make sure affected area remains covered by ointment.

Inactive Ingredients:

Beeswax, BHT, Chamomilla Recutita (Chamomile) Oil, Helianthus Annus (Sunflower) Oil, Prunus Amygdalus Dulcis (Sweet Almond) Oil.